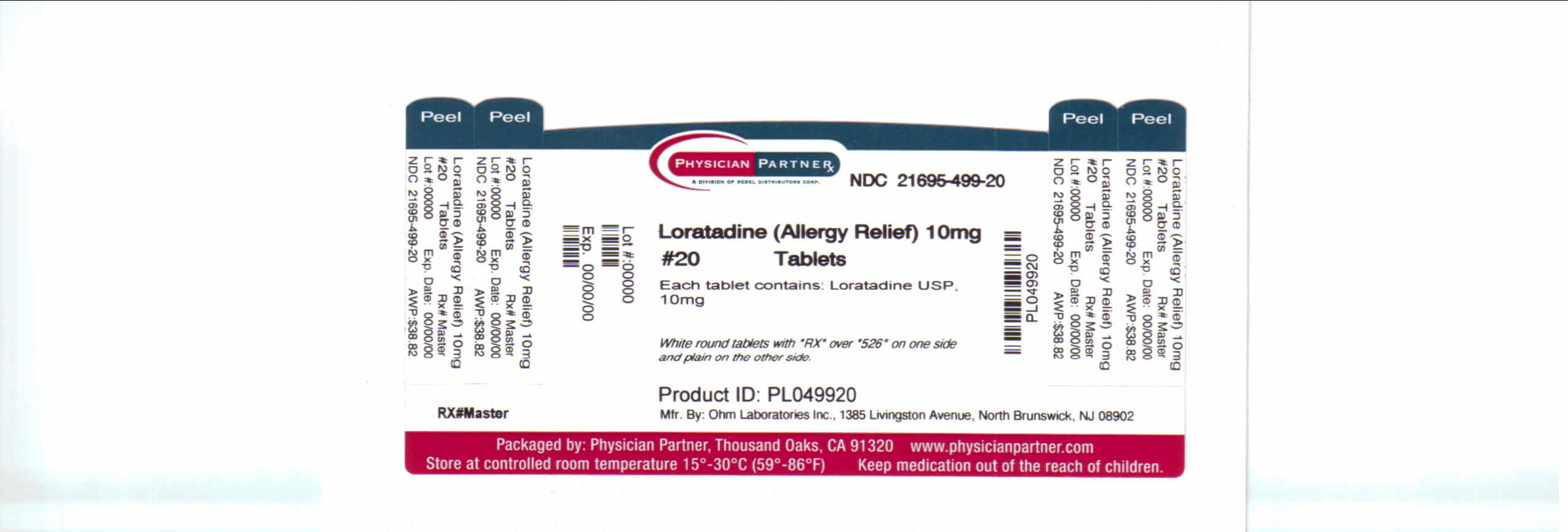 DRUG LABEL: Loratadine
NDC: 21695-499 | Form: TABLET
Manufacturer: Rebel Distributors Corp
Category: otc | Type: HUMAN OTC DRUG LABEL
Date: 20110209

ACTIVE INGREDIENTS: LORATADINE 10 mg/1 1
INACTIVE INGREDIENTS: STARCH, CORN; LACTOSE MONOHYDRATE; MAGNESIUM STEARATE; STARCH, CORN

Loratadine Tablets

Active ingredient

Loratadine USP, 10 mg

Purpose

Antihistamine

Uses

temporarily relieves these symptoms due to hay fever or other upper respiratory allergies: · itching of the nose or throat · runny nose · itchy, watery eyes · sneezing

Warnings

Do not use if you have ever had an allergic reaction to this product or any of its ingredients.

Ask a doctor before use if you have

liver or kidney disease. Your doctor should determine if you need a different dose.

When using this product

do not take more than directed. Taking more than directed may cause drowsiness.

Stop use and ask a doctor if

an allergic reaction to thsi product occurs. Seek medical help right away.

If pregnant or breast-feeding,

ask a health professional before use.

Keep out of reach of children.

In case of overdose, get medical help or contact a Poison Control Center right away.

Directions

adults and children 6 years and over | 1 tablet daily; not more than 1 tablet in 24 hours
children under 6 years of age | ask a doctor
consumers with liver or kidney disease | ask a doctor

Other Information

store between 20 and 25°C (68 and 77°F) · protect from excessive moisture.

Inactive ingredients

corn starch, lactose monohydrate, magnesium stearate, pregelatinized starch

Questions?

call 1-800-406-7984

†This product is not manufactured or distributed by Schering-Plough Healthcare Products Inc., owner of the registered trademark Claritin®.

Manufactured by
Ohm Laboratories, Inc.
North Brunswick, NJ 08902

Repackaged by
Rebel Distributors Corp

Thousand Oaks, CA 91320